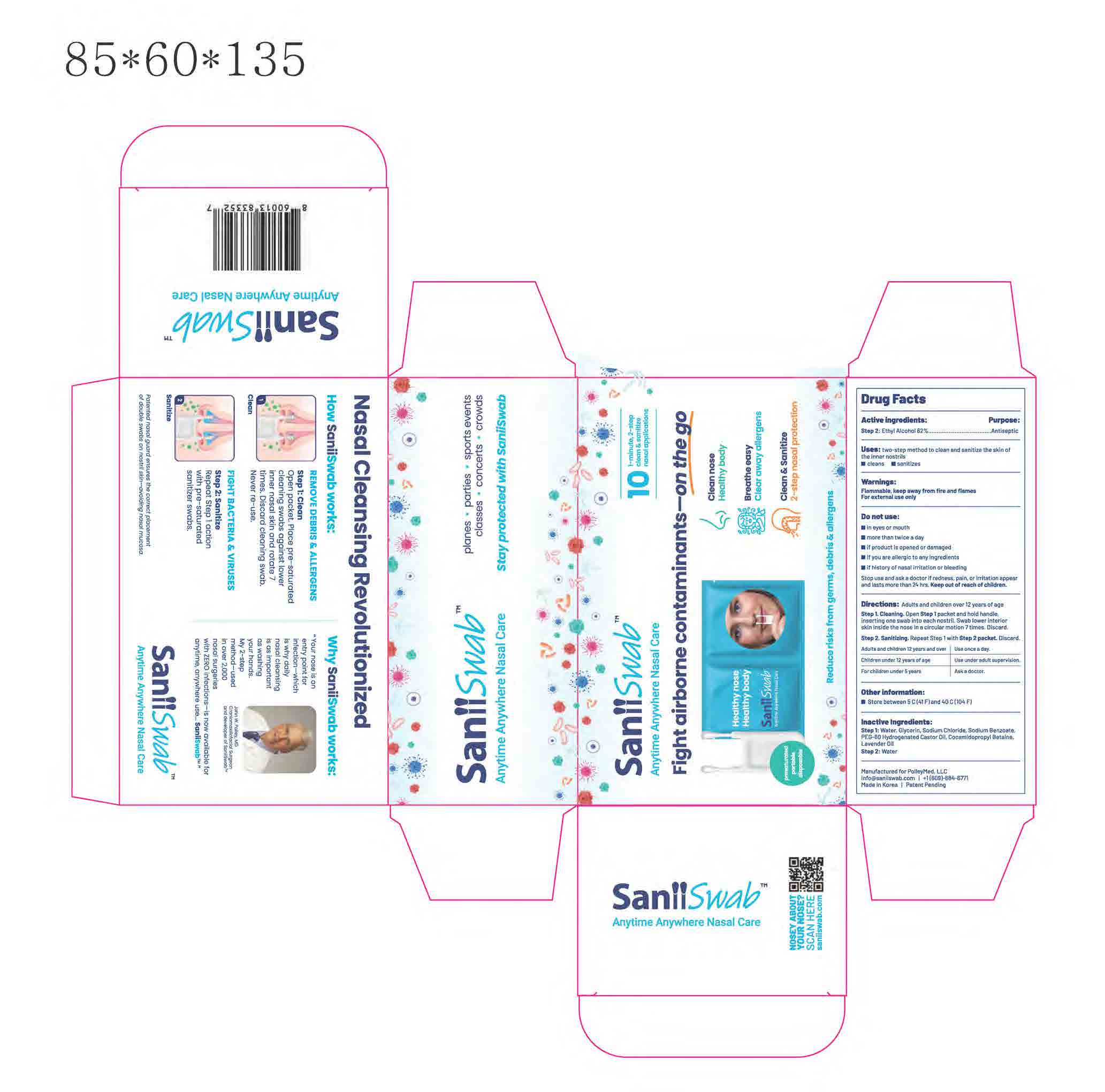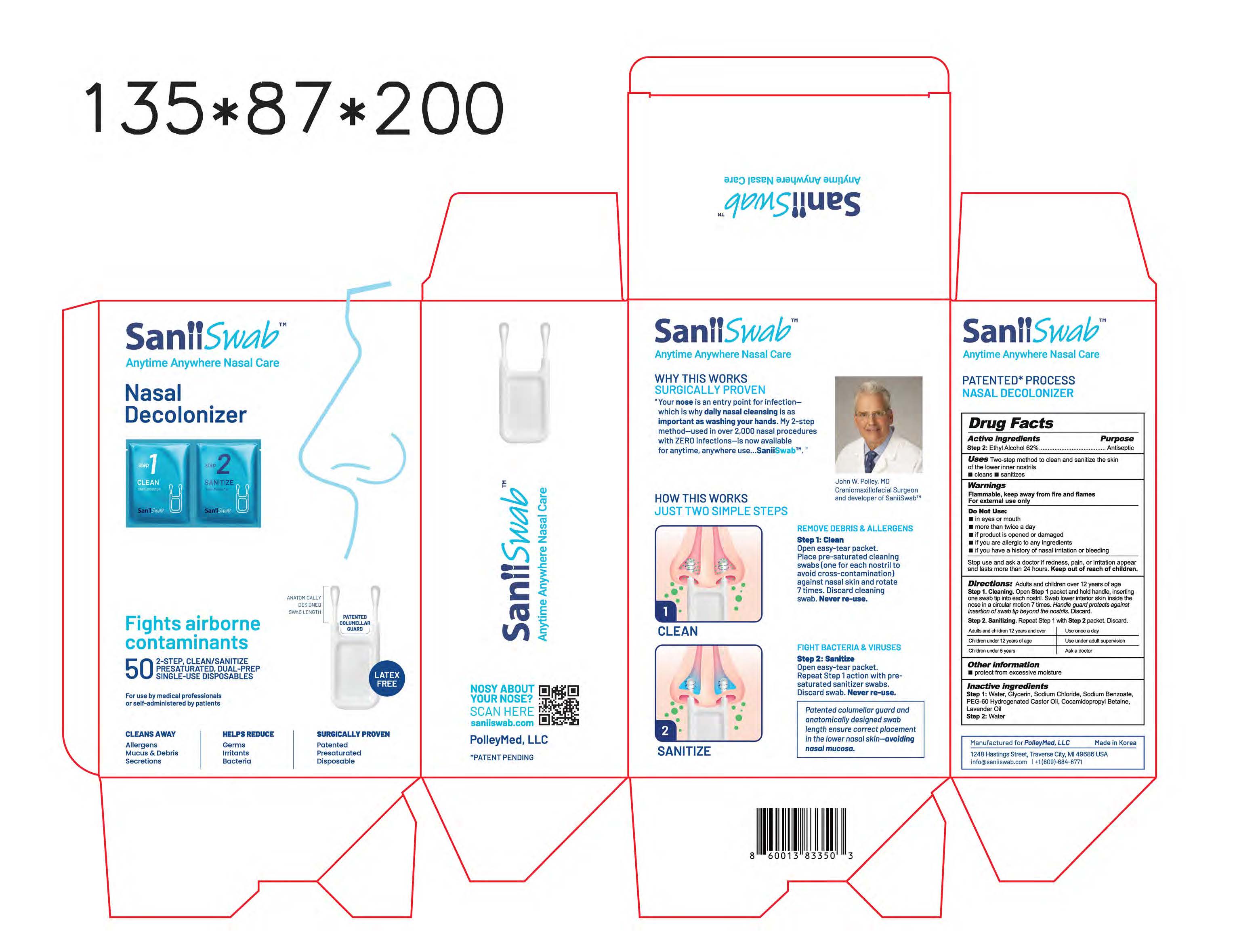 DRUG LABEL: SaniiSwab
NDC: 87051-001 | Form: SWAB
Manufacturer: PolleyMed LLC
Category: otc | Type: HUMAN OTC DRUG LABEL
Date: 20260214

ACTIVE INGREDIENTS: ALCOHOL 0.62 g/1 g
INACTIVE INGREDIENTS: SODIUM BENZOATE; GLYCERIN; WATER; SODIUM CHLORIDE; PEG-60 HYDROGENATED CASTOR OIL; COCAMIDOPROPYL BETAINE; LAVENDER OIL

ACTIVE INGREDIENT

Step 2: Ethyl Alcohol 62%

PURPOSE

Antiseptic

INDICATIONS AND USAGE

Two-step method to clean and sanitize the skin of the lower inner nostrils

■ cleans ■ sanitizes

WARNINGS

Flammable, keep away from fire and flames
For external use only

Do Not Use:

- In eyes or mouth
- More than twice a day
- If product is opened or damaged
- If you are allergic to any ingredients
- If you have a history of nasal irritation or bleeding

Stop use and ask a doctor if redness, pain, or irritation appear and lasts more than 24 hours. Keep out of reach of children.

Keep out of reach of children.

DOSAGE AND ADMINISTRATION

Directions: Adults and children over 12 years of age
Step 1. Cleaning. Open Step 1 packet and hold handle, inserting one swab tip into each nostril. Swab lower interior skin inside the nose in a circular motion 7 times. Handle guard protects against insertion of swab tip beyond the nostrils. Discard.
Step 2. Sanitizing. Repeat Step 1 with Step 2 packet. Discard.

Adults and children 12 years and over | Use once a day
Children under 12 years of age | Use under adult supervision
Childen under 5 years | Ask a Doctor

OTHER SAFETY INFORMATION

- protect from excessive moisture

INACTIVE INGREDIENT

Step 1: Water, Glycerin, Sodium Chloride, Sodium Benzoate, PEG-60 Hydrogenated Castor Oil, Cocamidopropyl Betaine, Lavender Oil
Step 2: Water

OTHER SAFETY INFORMATION

■ Store between 5 C (41 F) and 40 C (104 F)